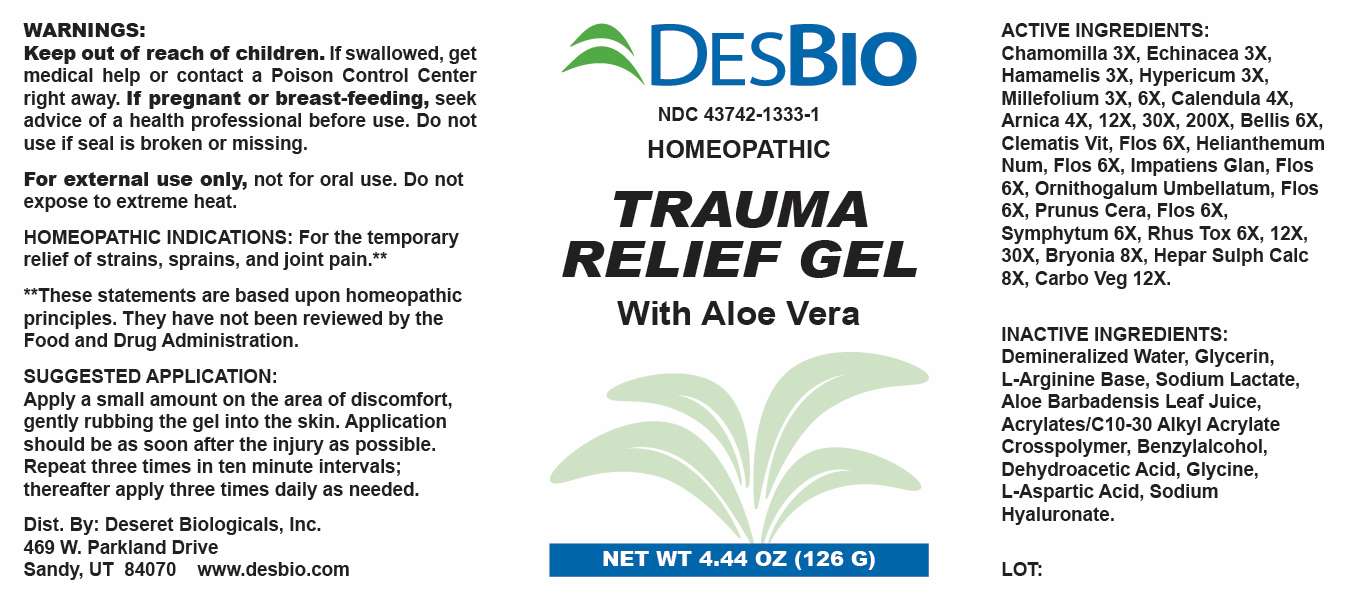 DRUG LABEL: Trauma Relief
NDC: 43742-1333 | Form: LIQUID
Manufacturer: Deseret Biologicals, Inc.
Category: homeopathic | Type: HUMAN OTC DRUG LABEL
Date: 20241022

ACTIVE INGREDIENTS: MATRICARIA CHAMOMILLA WHOLE 3 [hp_X]/1 g; ECHINACEA ANGUSTIFOLIA WHOLE 3 [hp_X]/1 g; HAMAMELIS VIRGINIANA ROOT BARK/STEM BARK 3 [hp_X]/1 g; HYPERICUM PERFORATUM WHOLE 3 [hp_X]/1 g; ACHILLEA MILLEFOLIUM WHOLE 3 [hp_X]/1 g; CALENDULA OFFICINALIS FLOWERING TOP 4 [hp_X]/1 g; ARNICA MONTANA WHOLE 4 [hp_X]/1 g; ATROPA BELLADONNA 6 [hp_X]/1 g; BELLIS PERENNIS WHOLE 6 [hp_X]/1 g; HELIANTHEMUM NUMMULARIUM FLOWER 6 [hp_X]/1 g; IMPATIENS GLANDULIFERA FLOWER 6 [hp_X]/1 g; ORNITHOGALUM UMBELLATUM FLOWERING TOP 6 [hp_X]/1 g; PRUNUS CERASIFERA FLOWER 6 [hp_X]/1 g; COMFREY ROOT 6 [hp_X]/1 g; TOXICODENDRON PUBESCENS LEAF 6 [hp_X]/1 g; BRYONIA ALBA ROOT 8 [hp_X]/1 g; CALCIUM SULFIDE 8 [hp_X]/1 g; ACTIVATED CHARCOAL 12 [hp_X]/1 g
INACTIVE INGREDIENTS: WATER; GLYCERIN; ARGININE; SODIUM PYRROLIDONE CARBOXYLATE; ALOE VERA LEAF; CARBOMER INTERPOLYMER TYPE A (ALLYL SUCROSE CROSSLINKED); BENZYL ALCOHOL; DEHYDROACETIC ACID; GLYCINE; ASPARTIC ACID; HYALURONIC ACID

DRUG FACTS:

ACTIVE INGREDIENTS:

Chamomilla 3X, Echinacea 3X, Hamamelis Virginiana 3X, Hypericum Perforatum 3X, Millefolium 3X, 6X, Calendula Officinalis 4X, Arnica Montana 4X, 12X, 30X, 200X, Bellis Perennis 6X, Clematis Vitalba, Flos 6X, Helianthemum Nummularium, Flos 6X, Impatiens Glandulifera, Flos 6X, Ornithogalum Umbellatum, Flos 6X, Prunus Cerasifera, Flos 6X, Symphytum Officinale 6X, Rhus Tox 6X, 12X, 30X, Bryonia (Alba) 8X, Hepar Sulphuris Calcareum 8X, Carbo Vegetabilis 12X.

PURPOSE:

For the temporary relief of strains, sprains, and joint pain.**

**These statements are based upon homeopathic principles. They have not been reviewed by the Food and Drug Administration.

WARNINGS:

Keep out of reach of children. If swallowed, get medical help or contact a Poison Control Center right away.

If pregnant or breast-feeding, seek advice of a health professional before use.

Do not use if seal is broken or missing.

For external use only, not for oral use.

Do not expose to extreme heat.

KEEP OUT OF REACH OF CHILDREN:

If swallowed, get medical help or contact a Poison Control Center right away.

SUGGESTED APPLICATION:

Apply a small amount on the area of discomfort, gently rubbing the gel into the skin. Application should be as soon after the injury as possible. Repeat three times in ten minute intervals; thereafter apply three times daily as needed.

INDICATIONS:

For the temporary relief of strains, sprains, and joint pain.**

**These statements are based upon homeopathic principles. They have not been reviewed by the Food and Drug Administration.

INACTIVE INGREDIENTS:

Demineralized Water, Glycerin, L-Arginine Base, Sodium Lactate, Aloe Barbadensis Leaf Juice, Acrylates/C10-30 Alkyl Acrylate Crosspolymer, Benzylalcohol, Dehydroacetic Acid, Glycine, L-Aspartic Acid, Sodium Hyaluronate.

QUESTIONS:

Dist. By: Deseret Biologicals, Inc.
469 W. Parkland Drive
Sandy, UT 84070

www.desbio.com

PACKAGE LABEL DISPLAY:

DESBIO

NDC 43742-1333-1

HOMEOPATHIC

TRAUMA

RELIEF GEL

With Aloe Vera

NET WT 4.44 OZ (126 G)